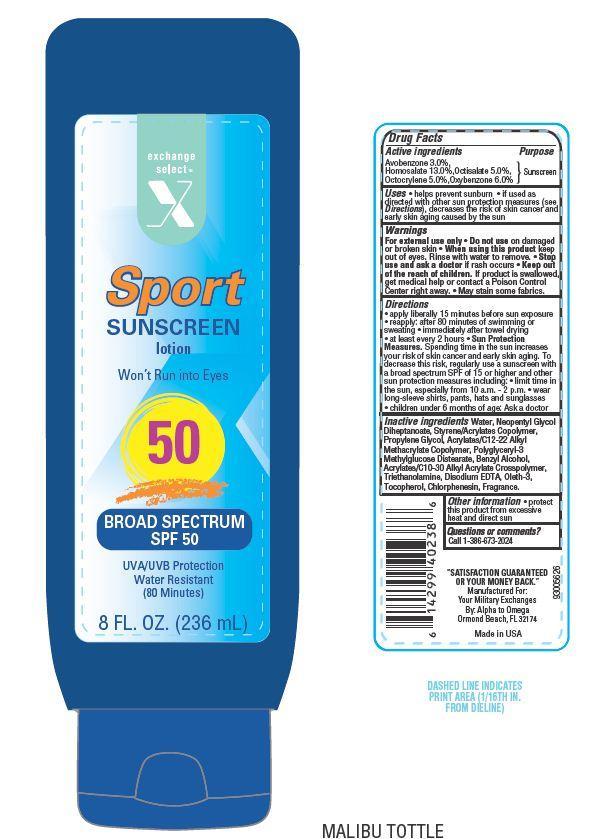 DRUG LABEL: EXCEL SPORT
NDC: 55301-018 | Form: LOTION
Manufacturer: ARMY AND AIR FORCE EXCHANGE SERVICE
Category: otc | Type: HUMAN OTC DRUG LABEL
Date: 20130806

ACTIVE INGREDIENTS: AVOBENZONE 3 g/100 g; HOMOSALATE 13 g/100 g; OCTISALATE 5 g/100 g; OCTOCRYLENE 5 g/100 g; OXYBENZONE 6 g/100 g
INACTIVE INGREDIENTS: WATER; NEOPENTYL GLYCOL DIHEPTANOATE; PROPYLENE GLYCOL; TROLAMINE; EDETATE DISODIUM; OLETH-3; TOCOPHEROL; BENZYL ALCOHOL; CHLORPHENESIN

Drug Facts

Active ingredients

Avobenzone 3.0%

Homosalate 13.0%

Octisalate 5.0%

Octocrylene 5.0%

Oxybenzone 6.0%

Uses

- Helps prevent sunburn
- If used as directed with other sun protection measures (see Directions), decrease the risk of skin cancer and early skin aging caused by the sun.

Warnings

For external use only. Do not use on damaged or broken skin

When using this product

- keep out of eyes. Rinse with water to remove

Stop use and ask a doctor if

- rash occurs

KEEP OUT OF REACH OF CHILDREN

Keep out of the reach of children. If swallowed get medical help or contact a Poison Control Center right away. May stain some fabrics.

Directions

- apply liberally 15 minutes before sun exposure
- reapply
- after 80 minutes of swimming or sweating
- immediately after towel drying
- at least every 2 hours
- Sun Protection Measures: Spending time in the sun increases your risk of skin cancer and early skin aging. To decrease this risk, regularly use a sunscreen with a broad spectrum SPF of 15 or higher and other sun protection measures including:
- limit time in the sun, especially from 10 a.m. - 2 p.m.
- wear long-sleeve shirts, pants, hats and sunglasses
- children under 6 months of age: Ask a doctor

Other information

- protect this product from excessive heat and direct sun

Inactive ingredients

Water, Neopentyl Glycol Diheptanoate, Styrene/Acrylates Copolymer, Propylene Glycol, Acrylates/C12-22 Alkyl Methacrylate Copolymer, Benzyl Alcohol, Polyglyceryl-3 Methylglucose Distearate, Acrylates/C10-30 Alkyl Acrylate Crosspolymer, Triethanolamine, Disodium EDTA, Tocopherol, Oleth-3, Chlorphenesin, Fragrance.

Principal Display Panel

exchange select

X

Sport SUNSCREEN

lotion

Won't Run into Eyes

50

BROAD SPECTRUM SPF 50

UVA/UVB Protection

Water Resistant

(80 Minutes)

8 FL. OZ. (236 mL)

Purpose

Sunscreen

Questions or comments?

Call 1-386-673-2024